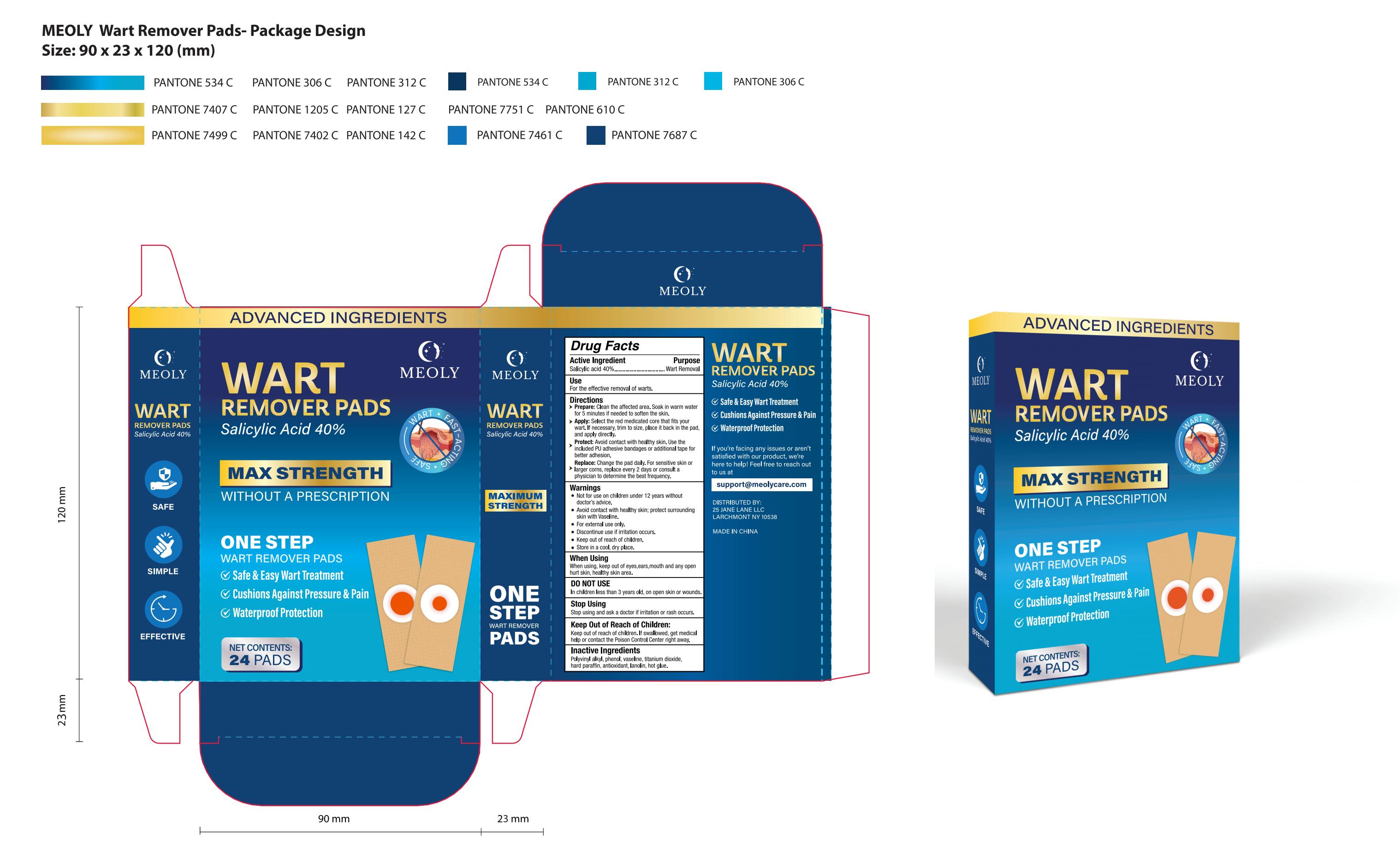 DRUG LABEL: MEOLY Wart Remover Pads
NDC: 83818-010 | Form: PATCH
Manufacturer: Shenzhen Xinxin Yunhai Technology Co., Ltd.
Category: otc | Type: HUMAN OTC DRUG LABEL
Date: 20250217

ACTIVE INGREDIENTS: SALICYLIC ACID 40 g/100 1
INACTIVE INGREDIENTS: PARAFFIN; C18-38 ALKYL HYDROXYSTEAROYL STEARATE; ANTIOXIDANT 119; PHENOL; TITANIUM DIOXIDE; VASOPRESSIN

83818-010

Active Ingredient

Salicylic acid 40.00%

Purpose

Wart Removal

Use

For the effective removal of warts.

Warnings

Not for use on children under 12 years withoutdoctor's advice.
Avoid contact with healthy skin; protect surroundingskin with Vaseline.
For external use only.
Discontinue use if irritation occurs.
Keep out of reach of children.
Store in a cool, dry place.

Do not use

In children less than 3 years old, on open skin or wounds.

When Using

When using, keep out of eyes,ears,mouth and any openhurt skin, healthy skin area.

Stop Use

Stop using and ask a doctor if irritation or rash occurs.

Ask Doctor

Stop using and ask a doctor if irritation or rash occurs.

Keep Oot Of Reach Of Children

Keep out of reach of children. lf swallowed, get medicahelp or contact the Poison Control Center right away.

Directions

Not for use on children under 12 years withoutdoctor's advice.Avoid contact with healthy skin; protect surroundingskin with Vaseline.
For external use only.
Discontinue use if irritation occurs.
Keep out of reach of children.
Store in a cool, dry place.

Other information

store between 59° and 86°F (15°C and 30°C)

Inactive ingredients

Polyvinyl alkyl, phenol, vaseline, titanium dioxidehard paraffin, antioxidant, lanolin, hot glue.

Questions

support@meolycare.com